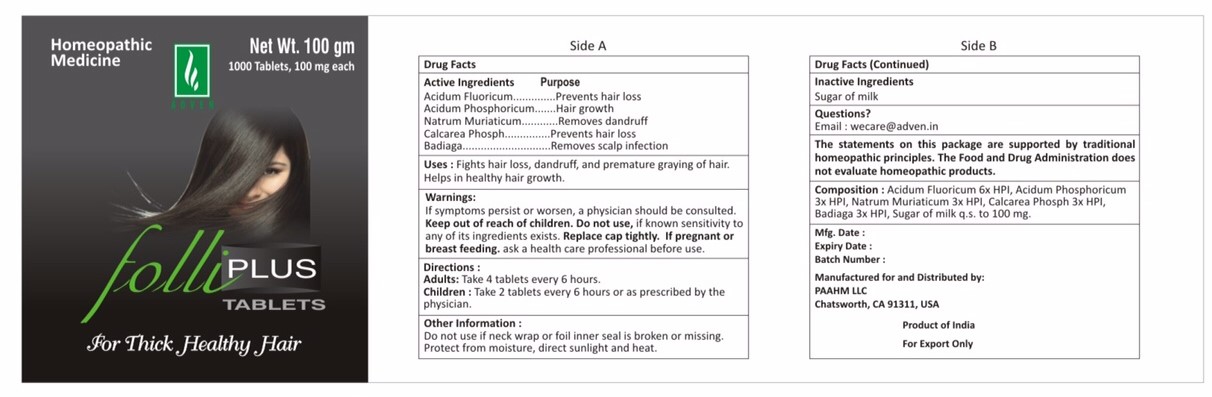 DRUG LABEL: folli plus
NDC: 69825-002 | Form: TABLET
Manufacturer: Adven Biotech Private Limited
Category: homeopathic | Type: HUMAN OTC DRUG LABEL
Date: 20160415

ACTIVE INGREDIENTS: PHOSPHORIC ACID 3 [hp_X]/1 mg; HYDROFLUORIC ACID 6 [hp_X]/1 mg; CALCIUM PHOSPHATE 3 [hp_X]/1 mg; SPONGILLA LACUSTRIS 3 [hp_X]/1 mg; SODIUM CHLORIDE 3 [hp_X]/1 mg
INACTIVE INGREDIENTS: LACTOSE

Folli Plus Tablets

ACTIVE INGREDIENT

Acidum Flouricum, Acidum Phosphoricum, Natrum Muriaticum, Calcarea, Badiaga

DOSAGE AND ADMINISTRATION

Adults: Take 4 tablets every 6 hours.

Children under 18 years: Take 2 tablets every 6 hours or as prescribed by the physician.

WARNINGS

If symptons persist or worsen, a physician should be consulted. Keep out of reach of children. Do not use, if known sentivity to any of its ingredients exists. Replace cap tightly. If pregnant or breast feeding, ask a health care professional before use.

PURPOSE

Fights hair loss, dandruff, and premature graying of hair. Helps in healthy hair growth.

INDICATIONS AND USAGE

Hair loss, dandruff, premature graying. Healthy hair growth.

INACTIVE INGREDIENT

Sugar of milk

Do not use if neck wrap or foil inner seal is broken or missing. Protect from moisture, direct sunlight and heat.